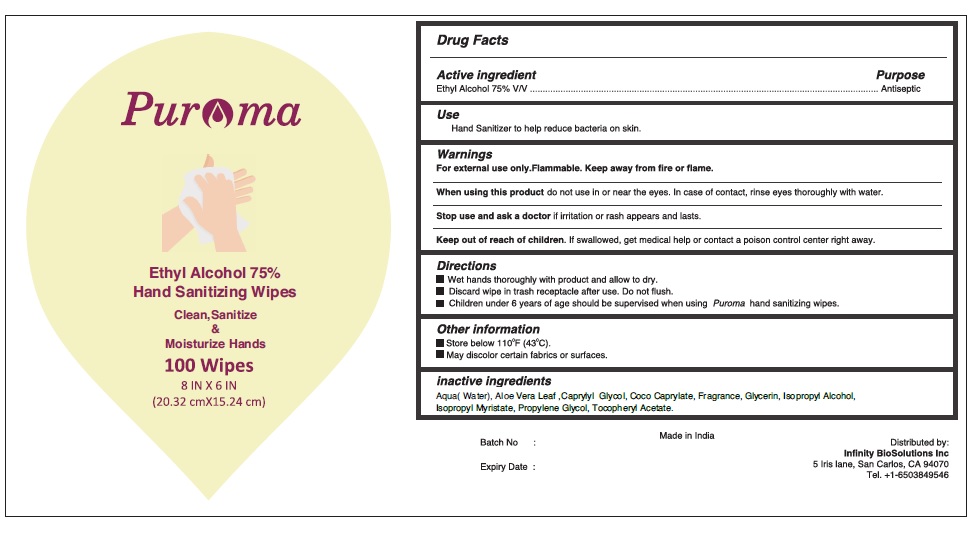 DRUG LABEL: PUROMA
NDC: 80948-001 | Form: CLOTH
Manufacturer: ZENITH MICRO CONTROL
Category: otc | Type: HUMAN OTC DRUG LABEL
Date: 20240201

ACTIVE INGREDIENTS: ALCOHOL 75 mL/100 mL
INACTIVE INGREDIENTS: WATER; ISOPROPYL ALCOHOL; GLYCERIN; ISOPROPYL MYRISTATE; .ALPHA.-TOCOPHEROL ACETATE; CAPRYLYL GLYCOL; ALOE VERA LEAF; PROPYLENE GLYCOL; COCO-CAPRYLATE; FRAGRANCE CLEAN ORC0600327

PUROMA Ethyl Alcohol 75% Antiseptic
wipes

Active Ingredient

Alcohol 75% V/V

Purpose

Antiseptic.

Warnings

- Flammable. Keep away from fire or flame.

For external use only.

- When using this productdo not use in or near the eyes. In case of contact, rinse eyes thoroughly with water.
- Stop use and ask a doctor ifirritation or rash appears and lasts.

Uses

Hand Sanitizer to help reduce bacteria on skin.

Directions

- Wet hands thoroughly with product and allow to dry.
- Discard wipe in trash receptacle after use. Do not flush.
- Children under 6 years of age should be supervised when using Puroma Hand Sanitizer wipe.

Keep out of reach of children.

If swallowed, get medical help or contact a poison control center right away.

Other information

- Store below 110°F (43°C)
- May discolor certain fabrics or surfaces

Inactive Ingredients

WATER,ISOPROPYL ALCOHOL ,GLYCERIN, ISOPROPYL MYRISTATE, ALPHA.-TOCOPHEROL ACETATE , CAPRYLYL GLYCOL, ALOE VERA LEAF, PROPYLENE GLYCOL, COCO-CAPRYLATE , FRAGRANCE